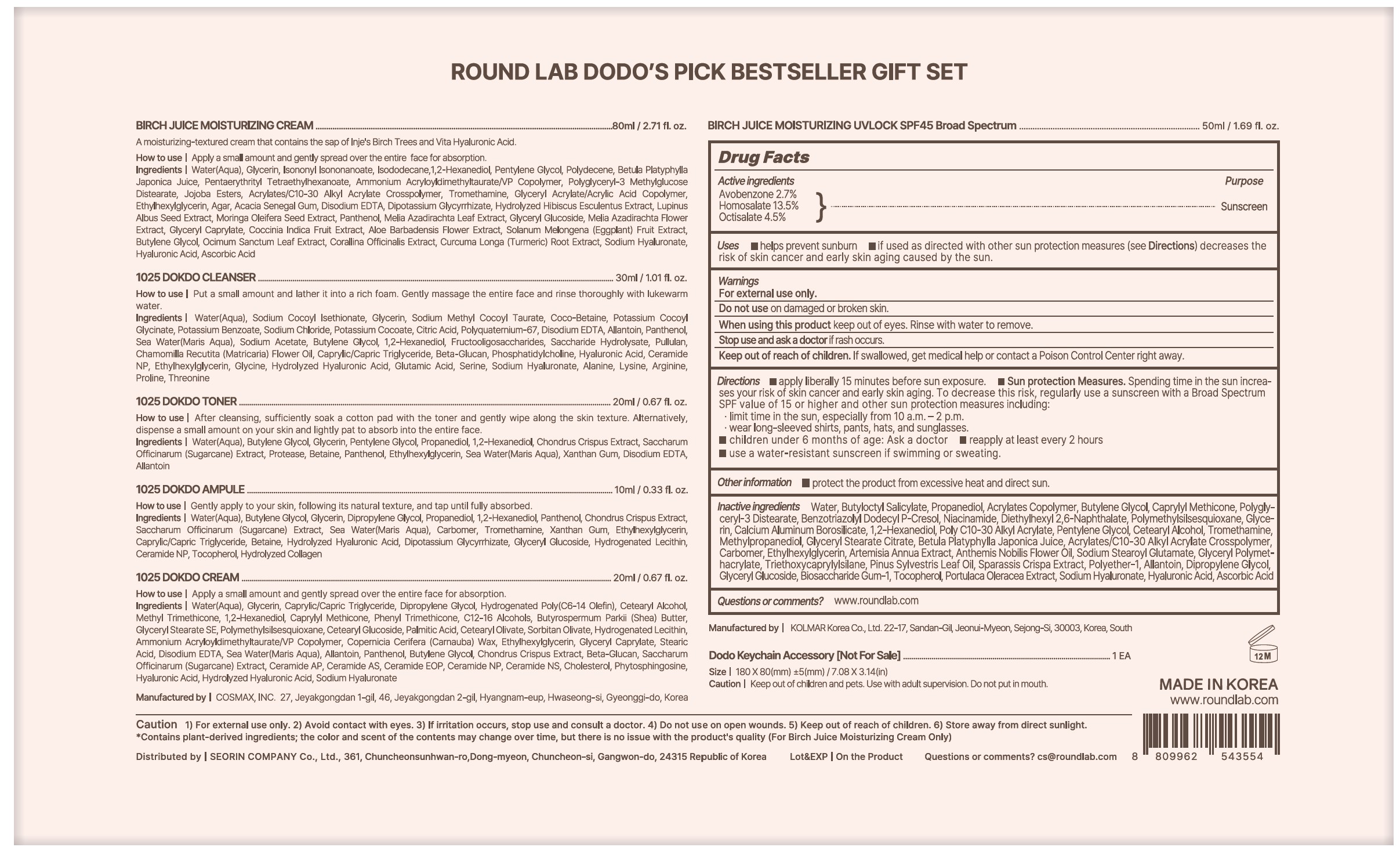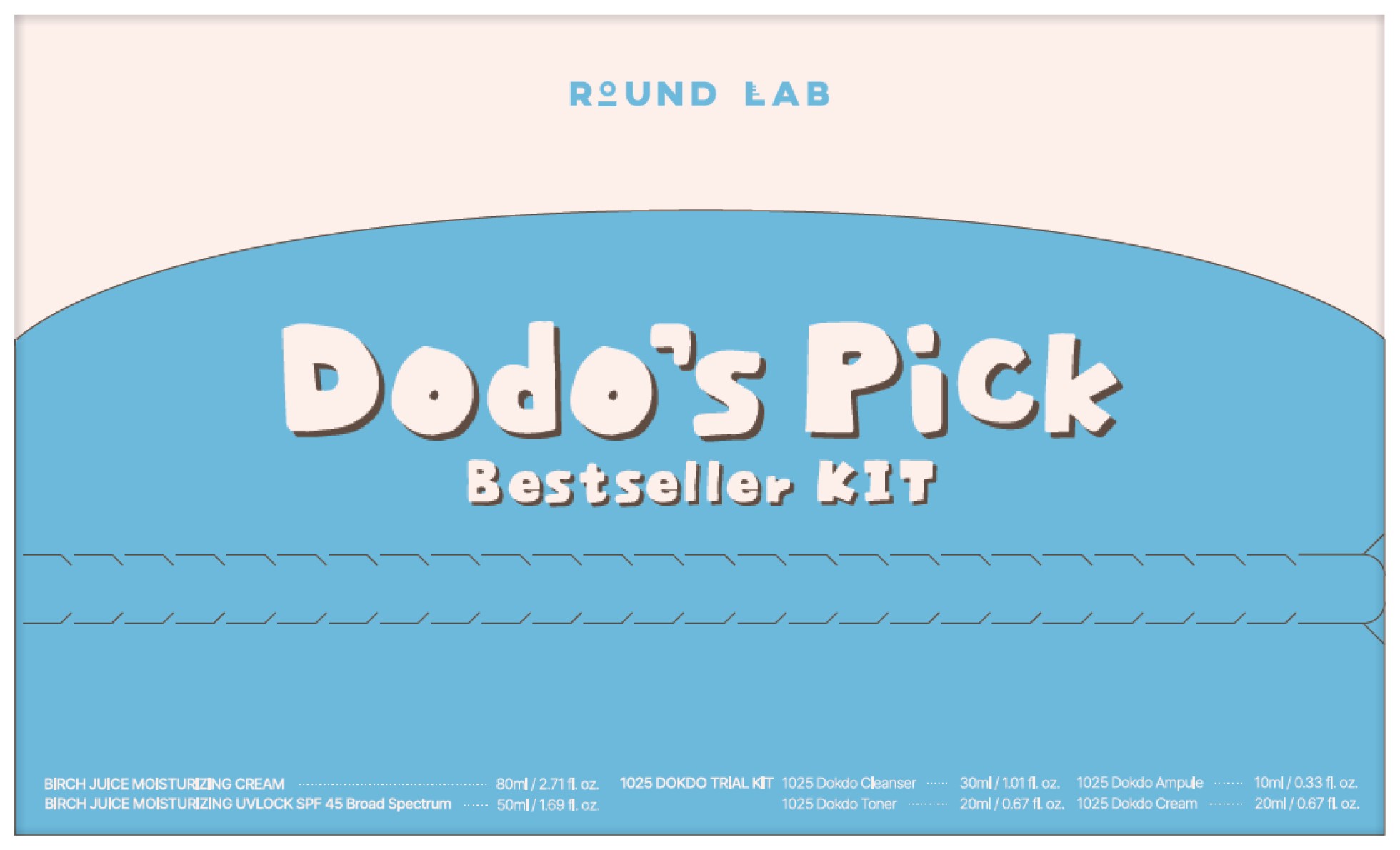 DRUG LABEL: Round Lab Dodo s Pick Bestseller Set
NDC: 84616-006 | Form: KIT | Route: TOPICAL
Manufacturer: SEORIN COMPANY Co., Ltd.
Category: otc | Type: HUMAN OTC DRUG LABEL
Date: 20250902

ACTIVE INGREDIENTS: HOMOSALATE 13.5 g/100 mL; OCTISALATE 4.5 g/100 mL; AVOBENZONE 2.7 g/100 mL
INACTIVE INGREDIENTS: 1,2-HEXANEDIOL; TOCOPHEROL; CHAMAEMELUM NOBILE FLOWER OIL; HYALURONIC ACID; BIOSACCHARIDE GUM-1; CALCIUM ALUMINUM BOROSILICATE; ARTEMISIA ANNUA LEAF; BENZOTRIAZOLYL DODECYL P-CRESOL; SPARASSIS CRISPA FRUITING BODY; CETOSTEARYL ALCOHOL; ETHYLHEXYLGLYCERIN; ALLANTOIN; CARBOMER HOMOPOLYMER, UNSPECIFIED TYPE; HYALURONATE SODIUM; GLYCERYL STEARATE CITRATE; GLYCERYL POLYMETHACRYLATE (300000 MPA.S); PROPANEDIOL; BUTYLENE GLYCOL; POLYGLYCERYL-3 DISTEARATE; DIETHYLHEXYL 2,6-NAPHTHALATE; NIACINAMIDE; SODIUM STEAROYL GLUTAMATE; TRIETHOXYCAPRYLYLSILANE; WATER; ASCORBIC ACID; PINE NEEDLE OIL (PINUS SYLVESTRIS); BEHENYL ACRYLATE POLYMER; TROMETHAMINE; PURSLANE; BUTYL ACRYLATE/METHYL METHACRYLATE/METHACRYLIC ACID COPOLYMER (18000 MW); BETULA PLATYPHYLLA VAR. JAPONICA RESIN; CAPRYLYL TRISILOXANE; ACRYLATES/C10-30 ALKYL ACRYLATE CROSSPOLYMER (60000 MPA.S); DIPROPYLENE GLYCOL; PENTYLENE GLYCOL; GLYCERYL GLUCOSIDE; POLYETHER-1 (2800 MPA.S); BUTYLOCTYL SALICYLATE; POLYMETHYLSILSESQUIOXANE (4.5 MICRONS); GLYCERIN; METHYLPROPANEDIOL

Round Lab Dodo's Pick Bestseller Set

Active Ingredients

Avobenzone 2.7%

Homosalate 13.5%

Octisalate 4.5%

Purpose

Sunscreen

Uses

- helps prevent sunburn
- if used as directed with other sun protection measures (see Directions) decreases the risk of skin cancer and early skin aging cause by the sun.

Warnings

For external use only,

Do not use on damaged or broken skin.

When using this product keep out of eyes. Rinse with water to remove

Stop use and ask a doctor if rash occurs.

KEEP OUT OF REACH OF CHILDREN

Keep out of reach or children. If swallowed, get medical help or contact a Poison Control Center right away.

Directions

- apply liberally and evenly 15 minutes before sun exposure.

Sun protection measures.

Spending time in the sun increases your risk of skin cancer and early aging. To decrease this risk, regularly use a sunscreen with a Broad Spectrum SPF value of 15 or higher and other sun protection measures including: limit time in the sun, especially from 10 a.m. - 2 p.m., wear long-sleeved shirts, pants, hats, and sunglasses

- children under 6 months of age: Ask a doctor
- reapply at least every 2 hours.
- use a water-resistant sunscreen if swimming or sweating

Other Informatiom

protect the product from excessive heat and direct sun

Inactive Ingredients

Water, Butyloctyl Salicylate, Propanediol, Acrylates Copolymer, Butylene Glycol, Caprylyl Methicone, Polyglyceryl-3 Distearate, Benzotriazolyl Dodecyl P-Cresol, Niacinamide, Diethylhexyl 2,6-Naphthalate, Polymethylsisesquioxane, Glycerin, Calcium Aluminum Borosilicate, 1,2-Hexanediol, Poly C10-30 Alkyl Acrylate, Pentylene Glycol, Cetearyl Aloohol, Tromethamine, Methy propanediol, Glyceryl Stearate Citrate, Betula Platyphylla Japonica Juice, Acrylates/C10-30 Alkyl Acrylate Crosspolymer, Carbomer, Ethylhexylglycerin, Artemisia Annua Extract, Anthemis Nobilis Flower Oil, Sodium Stearoyl Glutamate, Glyceryl Polymethacrylate, Triethoxycaprylylsilane, Pinus Sylvestris Leaf Oil, Sparassis Crispa Extract, Polyether-1, Allantoin, Di-propylene Glycol, Glyceryl Glucoside, Biosaccharide Gum-1, Tocopherol, Portulaca Oleracea Extract, Sodium Hyaluronate, Hyaluronic Acid, Ascorbic Acid

Questions or comments?

www.roundlab.com

PACKAGE LABEL

1025 DOKDO TRIAL KIT

BIRCH JUICE MOISTURIZING CREAM..............................................80mL/2.71 fl.oz

BIRCH JUICE MOISTURIZING UVLOCK SPF 45 Broad Spectrum....50mL/1.69 fl.oz

1025 Dokdo Cleanser...........................................................................30mL/1.01 fl.oz

1025 Dokdo Toner................................................................................20mL/0.67 fl.oz

1025 Dokdo Ampule.............................................................................10mL/0.33 fl.oz

1025 Dokdo Cream..............................................................................20mL/0.67 fl.oz